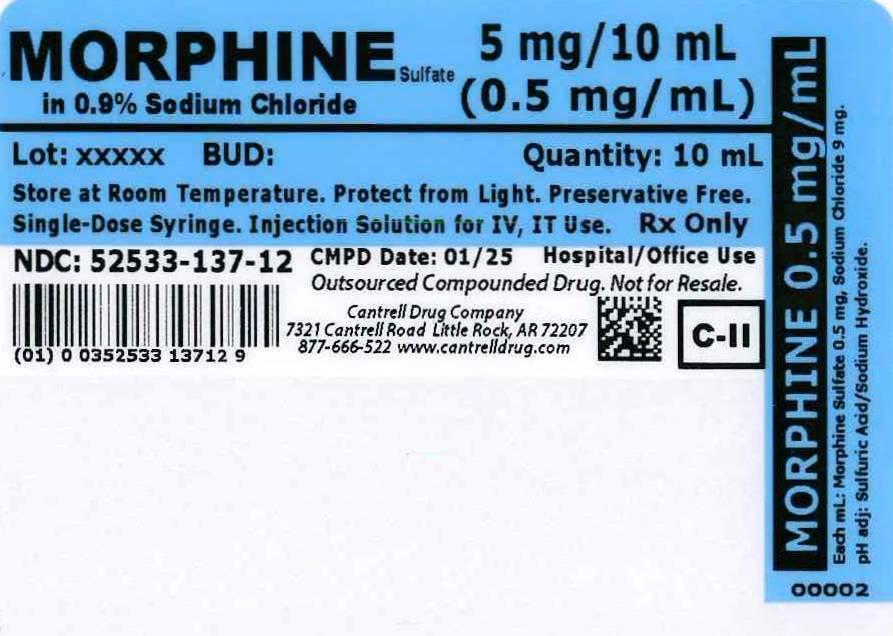 DRUG LABEL: Morphine Sulfate
NDC: 52533-137 | Form: INJECTION, SOLUTION
Manufacturer: Cantrell Drug Company
Category: prescription | Type: HUMAN PRESCRIPTION DRUG LABEL
Date: 20140502
DEA Schedule: CII

ACTIVE INGREDIENTS: MORPHINE SULFATE 0.5 mg/1 mL
INACTIVE INGREDIENTS: Sodium Chloride 9 mg/1 mL; Water

Morphine Sulfate 0.5 mg/mL in 0.9% Sodium Chloride 10 mL Syringe